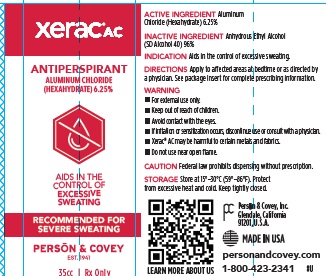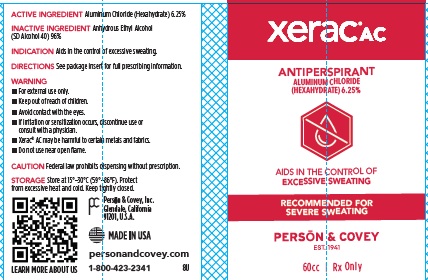 DRUG LABEL: Xerac AC
NDC: 0096-0709 | Form: LIQUID
Manufacturer: Person and Covey
Category: otc | Type: HUMAN OTC DRUG LABEL
Date: 20251128

ACTIVE INGREDIENTS: ALUMINUM CHLORIDE 0.0625 g/1 g
INACTIVE INGREDIENTS: ALCOHOL

Xerac AC

OTC - PURPOSE SECTION

For topical application as an antiperspirant (anhidrotic).

DOSAGE & ADMINISTRATION SECTION

Xerac AC when applied to the underarms, should be applied to absolutely dry skin. Only apply Xerac AC before bedtime, since medication should be kept on the skin for 6-8 hours. To reduce irritation, let the alcohol evaporate, leaving a thin film of antiperspirant on the skin. Wear a T-shirt, while sleeping to prevent medication from being rubbed off on the bed linens. Do not apply Xerac AC to broken, irritated or recently shaved skin. Wash the treated area next morning with soap and water. Do not apply other deodorants or antiperspirants while using Xerac AC.

WARNINGS SECTION

For external use only. Avoid contact with eyes. If contact occurs, wash eyes thoroughly with water. If irritation or sensitization occurs, discontinue use or contact a physician. Xerac AC may be harmful to cotton fibers and certain metals.

OTC - KEEP OUT OF REACH OF CHILDREN SECTION

Yes. If swallowed, get medical help or contact a Poison Control Center right away.

OTC - ACTIVE INGREDIENT SECTION

Aluminum Chloride Hexahydrate

INACTIVE INGREDIENT SECTION

Anhydrous ethanol

Indicatins and Usage Section

For patients suffering from hyperhidrosis, or patients whose jobs or sports activities cause excessive sweating that exacerbates other skin problems.